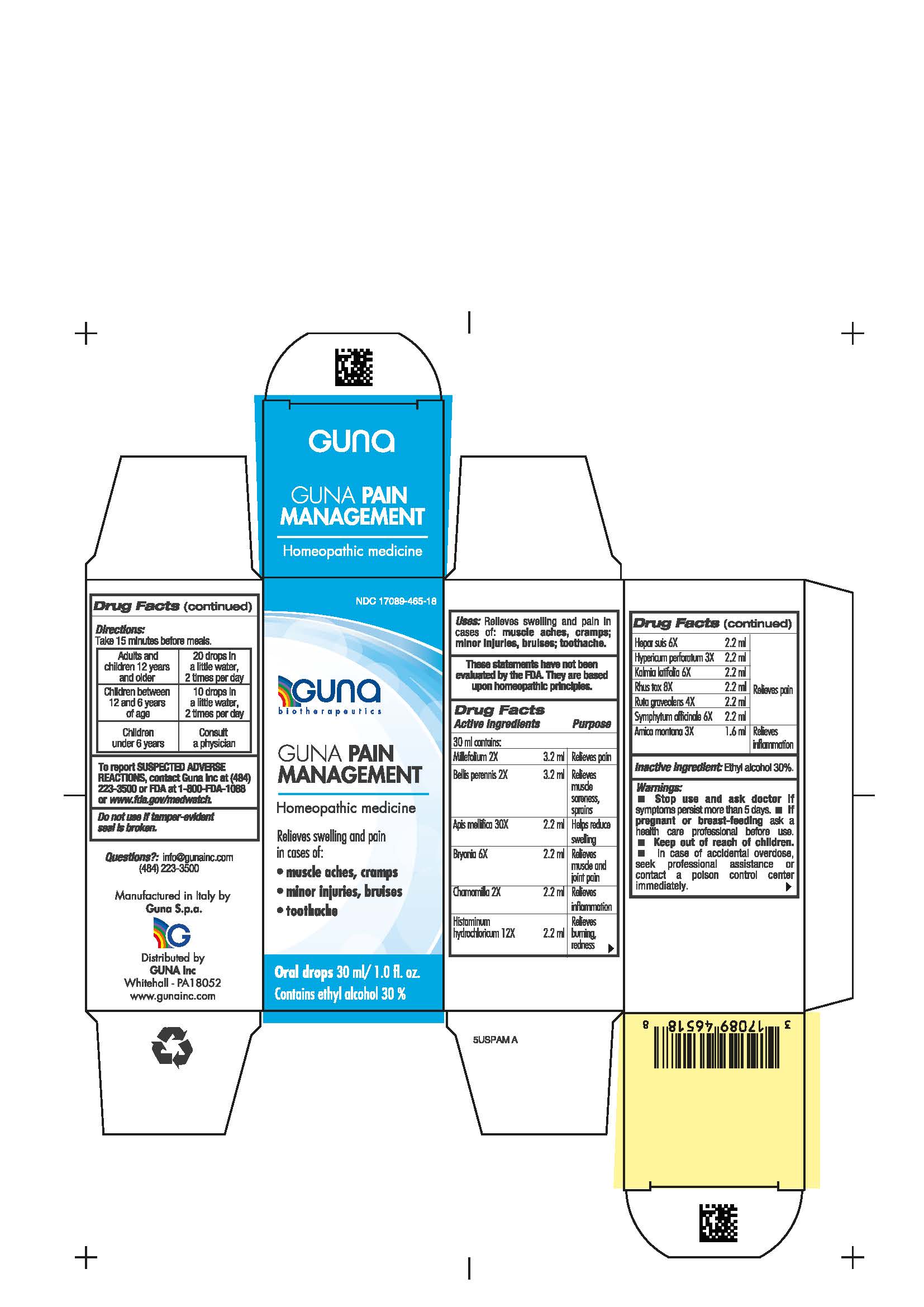 DRUG LABEL: GUNA PAIN MANAGEMENT
NDC: 17089-465 | Form: SOLUTION/ DROPS
Manufacturer: Guna spa
Category: homeopathic | Type: HUMAN OTC DRUG LABEL
Date: 20200915

ACTIVE INGREDIENTS: BRYONIA ALBA ROOT 6 [hp_X]/30 mL; HISTAMINE DIHYDROCHLORIDE 12 [hp_X]/30 mL; HYPERICUM PERFORATUM 3 [hp_X]/30 mL; ARNICA MONTANA WHOLE 3 [hp_X]/30 mL; PORK LIVER 6 [hp_X]/30 mL; BELLIS PERENNIS WHOLE 2 [hp_X]/30 mL; MATRICARIA CHAMOMILLA WHOLE 2 [hp_X]/30 mL; TOXICODENDRON PUBESCENS LEAF 8 [hp_X]/30 mL; RUTA GRAVEOLENS FLOWERING TOP 4 [hp_X]/30 mL; KALMIA LATIFOLIA LEAF 6 [hp_X]/30 mL; ACHILLEA MILLEFOLIUM WHOLE 2 [hp_X]/30 mL; COMFREY ROOT 6 [hp_X]/30 mL; APIS MELLIFERA 30 [hp_X]/30 mL
INACTIVE INGREDIENTS: ALCOHOL 9 mL/30 mL

GUNA PAIN MANAGEMENT

Inactive ingredient: Ethyl alcohol 30%.

QUESTIONS

info@gunainc.com
Tel. (484) 223-3500

WARNINGS

Keep out of reach of children.

INDICATIONS AND USAGE

Take 15 minutes before meals.

DIRECTIONS

Take 15 minutes before meals.

Adults and children twelve years and older: 20 drops in a little water, 2 times per day

Children between 12 years and 6 years of age: 10 drops in a little water, 2 times per day

Children under 6 years: consult a physician

PREGNANCY

If pregnant or breast-feeding ask a health care profesisonal before use.

WARNINGS

- Stop use and ask doctor if symptoms worsen or persist more than 5 days.
- If pregnant or breast-feeding ask a health care professional before use.
- Keep out of reach of children.
- In case of accidental overdose, seek professional assistance or contact a poison control center immediately
- Contains ethyl alcohol 30%

ACTIVE INGREDIENTS/PURPOSE

Millefolium 2X Relieves pain

Bellis perennis 2X Relieves muscle soreness, sprains

Apis mellifica 30X Helps reduce swelling

Bryonia 6X Relieves muscle and joint pain

Chamomilla 2X Relieves inflammation

Histaminum hydroc. 12X Relieves burning, redness

Hepar suis 6X Relieves pain

Hypericum perf. 3X Relieves pain

Kalmia latifolia 6X Relieves pain

Rhus tox 8X Relieves pain

Ruta graveolens 4X Relieves pain

Symphytum officinale 6X Relieves pain

Arnica montana 3X Relieves inflammation

USES

Relieves swelling and pain in cases of:

- muscle aches, cramps
- minor injuries, bruises
- toothache